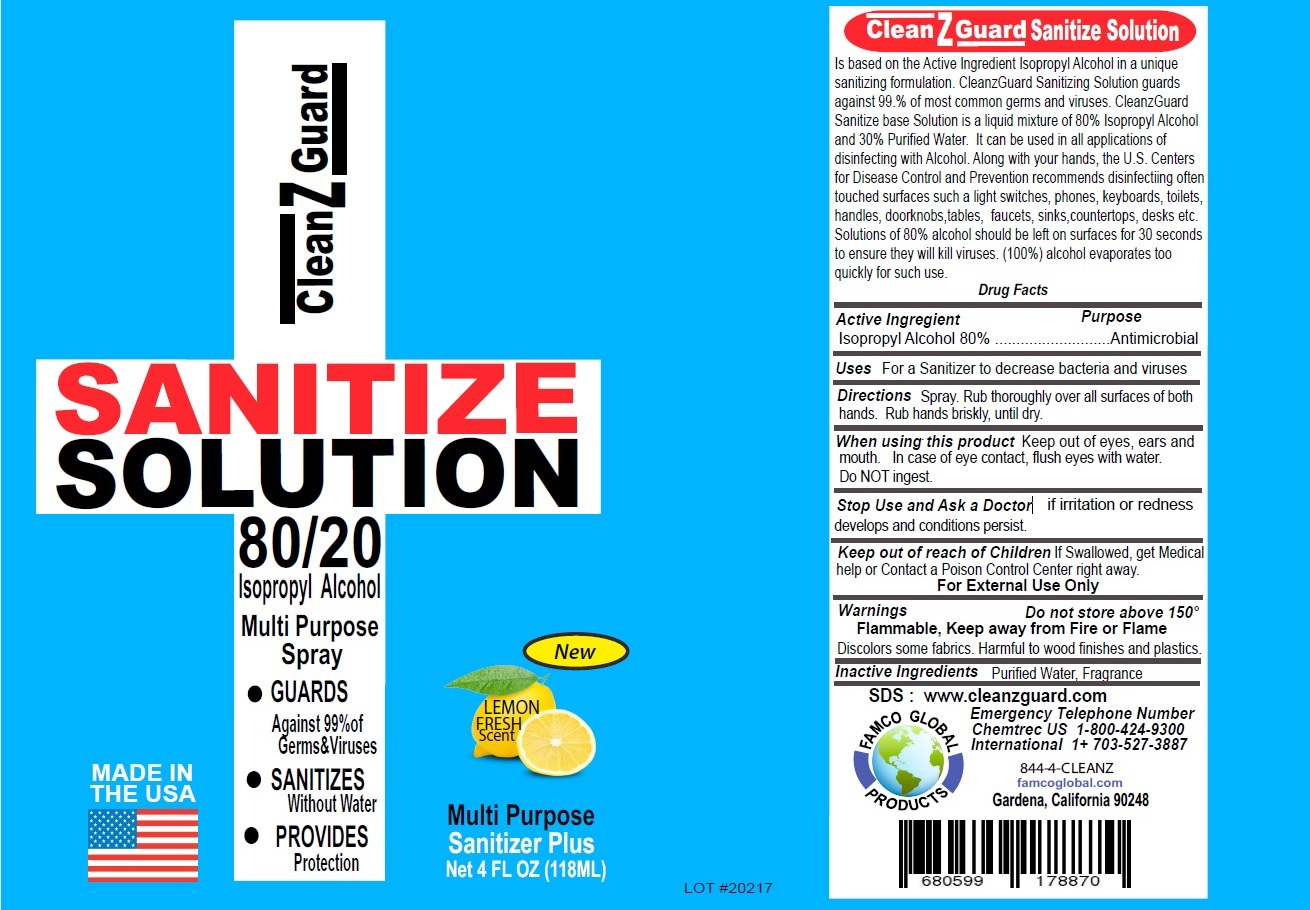 DRUG LABEL: CLEANZGUARD SANITIZE
NDC: 79743-230 | Form: SOLUTION
Manufacturer: Famco Global Llc
Category: otc | Type: HUMAN OTC DRUG LABEL
Date: 20200803

ACTIVE INGREDIENTS: ISOPROPYL ALCOHOL 80 mL/100 mL
INACTIVE INGREDIENTS: WATER

CleanzGuard SANITIZE SOLUTION

Active Ingredient

Isopropyl Alcohol 80%

Purpose

Antimicrobial

Uses

For a Sanitizer to decrease bacteria and viruses

DOSAGE AND ADMINISTRATION

Directions Spray. Rub thoroughly over all surfaces of both hands. Rub hands briskly, until dry.

When using this product Keep out of eyes, ears and mouth. In case of eye contact, flush eyes with water.

Do NOT ingest.

Stop Use and Ask a Doctor if irritation or redness develops and conditions persist.

For External Use Only

Warnings

Flammable, Keep away from Fire or Flame

Keep out of reach of Children If Swallowed, get Medical help or Contact a Poison Control Center right away.

STORAGE AND HANDLING

Do not store above 150°

Discolors some fabrics. Harmful to wood finishes and plastics.

Inactive Ingredients Purified Water, Fragrance

80/20

Isopropyl Alcohol

Multi Purpose Spray

•GUARDS

Against 99%of Germs&Viruses

•SANITIZES

Without Water

•PROVIDES

Protection

MADE IN THE USA

New

LEMON FRESH Scent

Multi Purpose

Sanitizer Plus

Is based on the Active Ingredient Isopropyl Alcohol in a unique sanitizing formulation. CleanzGuard Sanitizing Solution guards against 99.% of most common germs and viruses. CleanzGuard Sanitize base Solution is a liquid mixture of 80% Isopropyl Alcohol and 30% Purified Water. It can be used in all applications of disinfecting with Alcohol. Along with your hands, the U.S. Centers for Disease Control and Prevention recommends disinfecting often touched surfaces such a light switches, phones, keyboards, toilets, handles, doorknobs, tables, faucets, sinks, countertops, desks etc. Solutions of 80% alcohol should be left on surfaces for 30 seconds to ensure they will kill viruses. (100%) alcohol evaporates too quickly for such use.

SDS : www.cleanzguard.com

FAMCO GLOBAL PRODUCTS

Emergency Telephone Number

Chemtrec US 1-800-424-9300

International 1+ 703-527-3887

844-4-CLEANZ

famcoglobal.com

Gardena, California 90248